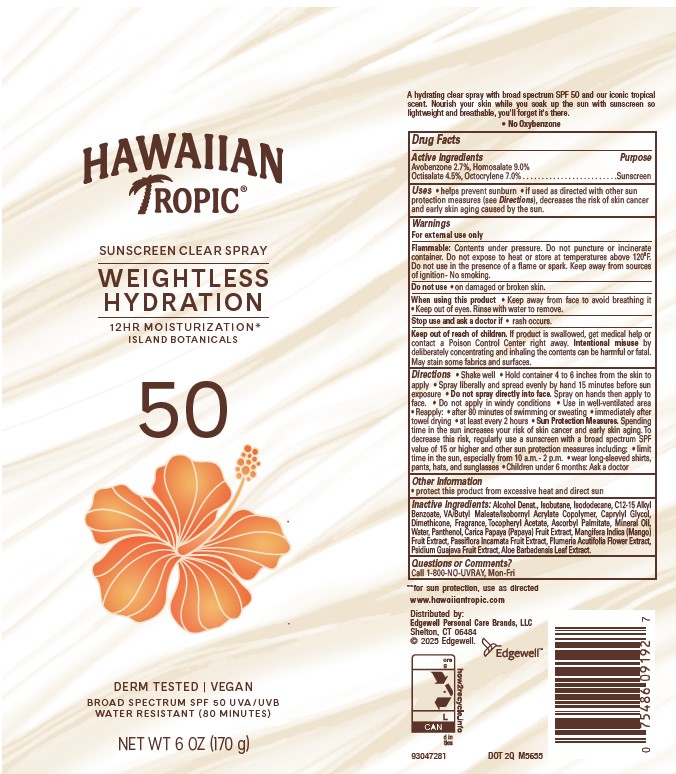 DRUG LABEL: HAWAIIAN TROPIC
NDC: 63354-232 | Form: AEROSOL, SPRAY
Manufacturer: Edgewell Personal Care Brands LLC
Category: otc | Type: HUMAN OTC DRUG LABEL
Date: 20251218

ACTIVE INGREDIENTS: HOMOSALATE 9 g/100 g; OCTOCRYLENE 7 g/100 g; OCTISALATE 4.5 g/100 g; AVOBENZONE 2.7 g/100 g
INACTIVE INGREDIENTS: MINERAL OIL; GLYCERYL OLEATE; ALOE VERA LEAF; PLUMERIA RUBRA FLOWER; GUAVA; ASCORBYL PALMITATE; CAPRYLYL GLYCOL; PASSIFLORA INCARNATA FRUIT; ISOBUTANE; ISODODECANE; WATER; ALKYL (C12-15) BENZOATE; ALPHA-TOCOPHEROL ACETATE; MANGO; DIMETHICONE; ALCOHOL; PANTHENOL; PAPAYA

Active Ingredients

Avobenzone 2.7%, Homosalate 9.0%, Octisalate 4.5%, Octocrylene 7.0%

Purpose

Sunscreen

Uses

• helps prevent sunburn • if used as directed with other sun protection measures (see Directions), decreases the risk of skin cancer and early skin aging caused by the sun.

Warnings

For external use only

Flammable: Contents under pressure. Do not puncture or incinerate container. Do not expose to heat or store at temperatures above 120oF. Do not use in the presence of a flame or spark. Keep away from sources of ignition - No smoking.

May stain some fabrics and surfaces.

Do not use

on damaged or broken skin.

When using this product

• Keep away from face to avoid breathing it • Keep out of eyes. Rinse with water to remove.

Stop use and ask a doctor

if rash occurs

Keep out of reach of children.

If product is swallowed, get medical help or contact a Poison Control Center right away. Intentional misuse by deliberately concentrating and inhaling the contents can be harmful or fatal. May stain some fabrics and surfaces.

Directions

• Shake well • Hold container 4 to 6 inches from the skin to apply • Spray liberally and spread evenly by hand 15 minutes before sun exposure • Do not spray directly into face. Spray on hands then apply to face. • Do not apply in windy conditions • Use in well-ventilated area • Reapply: • after 80 minutes of swimming or sweating • immediately after towel drying • at least every 2 hours • Sun Protection Measures. Spending time in the sun increases your risk of skin cancer and early skin aging. To decrease this risk, regularly use a sunscreen with a broad spectrum SPF value of 15 or higher and other sun protection measures including: • limit time in the sun, especially from 10 a.m. - 2 p.m. • wear long-sleeved shirts, pants, hats, and sunglasses • Children under 6 months: Ask a doctor

Other Information

• protect this product from excessive heat and direct sun

Inactive Ingredients:

Alcohol Denat., Isobutane, Isododecane, C12-15 Alkyl Benzoate, VA/Butyl Maleate/Isobornyl Acrylate Copolymer, Caprylyl Glycol, Dimethicone, Fragrance, Tocopheryl Acetate, Ascorbyl Palmitate, Mineral Oil, Water, Panthenol, Carica Papaya (Papaya) Fruit Extract, Mangifera Indica (Mango) Fruit Extract, Passiflora Incarnata Fruit Extract, Plumeria Acutifolia Flower Extract, Psidium Guajava Fruit Extract, Aloe Barbadensis Leaf Extract.

Questions or Comments?

Call 1-800-NO-UVRAY, Mon-Fri

Principal Display Panel

HAWAIIAN
TROPIC (R)
SUNSCREEN CLEAR SPRAY
WEIGHTLESS
HYDRATION
12HR MOISTURIZATION*
ISLAND BOTANICALS
50
DERM TESTED | VEGAN
BROAD SPECTRUM SPF 50 UVA/UVB
WATER RESISTANT (80 MINUTES)
NET WT 6 OZ (170 g)